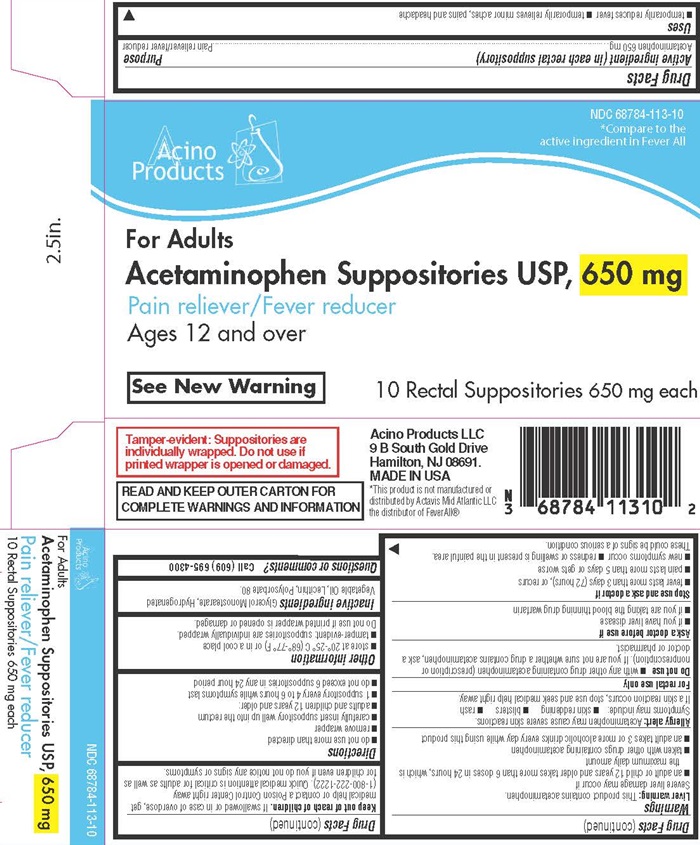 DRUG LABEL: ACETAMINOPHEN
NDC: 68784-113 | Form: SUPPOSITORY
Manufacturer: Acino Products, LLC
Category: otc | Type: HUMAN OTC DRUG LABEL
Date: 20160203

ACTIVE INGREDIENTS: ACETAMINOPHEN 650 mg/1 1
INACTIVE INGREDIENTS: GLYCERYL MONOSTEARATE; FAT, HARD; HYDROGENATED SOYBEAN LECITHIN; POLYSORBATE 80

Acetaminophen Suppositories - 113 DPL

Drug facts Active ingredient (in each suppository)

Acetaminophen 650 mg

Purpose

Pain reliever/fever reducer

Keep out of reach of children.

If swallowed or in case of overdose, get medical help or contact a Poison Control Center right away (1-800-222-1222) Quick medical attention is critical for adults as well as for children even if you do not notice any signs or symptoms.

Uses

- temporarily reduces fever
- temporarily relieves minor aches, pains and headache

Warnings

Liver warning: This product contains acetaminophen.

Severe liver damage may occur if

- an adult or child 12 years and older takes more than 6 doses in 24 hours, which is the maximum daily amount
- taken with other drugs containing acetaminophen
- an adult takes 3 or more alcoholic drinks every day while using this product

Allergy alert: Acetaminophen may cause severe skin reactions.

Symptoms may include:

- skin reddening
- blisters
- rash

If a skin reaction occurs, stop use and seek medical help right away.

For rectal use only.

Do not use

- with any other drug containing acetaminophen (prescription or nonprescription). If you are not sure whether a drug contains acetaminophen, ask a doctor or pharmacist.

Ask a doctor before use if

- if you have liver disease
- if you are taking the blood thinning drug warfarin

Stop use and ask a doctor if

- fever lasts more than 3 days (72 hours), or recurs.
- pain lasts more than 5 days or gets worse.
- new symptoms occur.
- redness or swelling is present in the painful area.

These could be signs of a serious condition.

Directions

- do not use more than directed
- remove wrapper
- carefully insert suppository well up into the rectum
- adults and children 12 years and older:
- 1 suppository every 4 to 6 hours while symptoms last
- do not exceed 6 suppositories in any 24 hour period

Other information

- store at 20°-25°C (68°-77°F) or in a cool place
- tamper evident suppositories are individually wraped.

Do not use if printed wrapper is open or damaged.

Inactive ingredients

Glycerol Monostearate, Hydrogenated Vegetable Oil, Lecithin, Polysorbate 80

Questions or comments?

Call (609-695-4300)

Acetaminophen Suppositories For Adults product label

Acino Products

NDC 68784-113-10

*Compare to the active ingredient in Fever All

For Adults

Acetaminophen Suppositories USP, 650 mg

Pain reliever/Fever reducer

Ages 12 and over

See New Warning

10 Rectal Suppositories 650 mg each

Tamper-evident: Suppositories are individually wrapped. Do not use if printed wrapper is opened or damaged

READ AND KEEP OUTER CARTON FOR COMPLETE WARNINGS AND INFORMATION

Acino Products LLC

9B South Gold Drive

Hamilton, NJ 08691.

MADE IN THE USA

*This product is not manufactured or distributed by Acino Mid Atlantic LLC the distributed of Fever All®